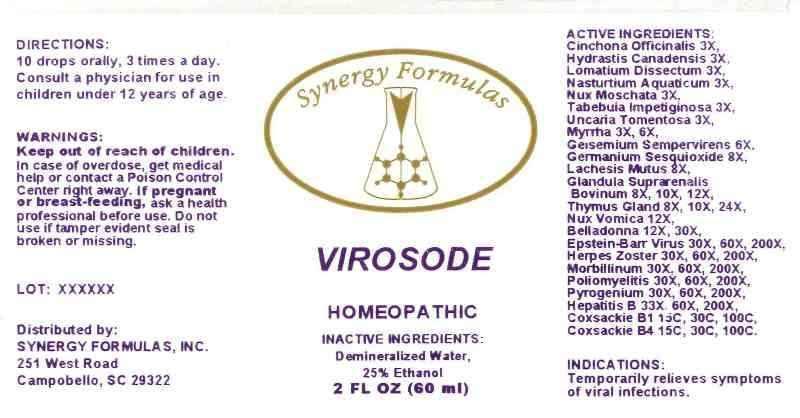 DRUG LABEL: Virosode
NDC: 43772-0007 | Form: LIQUID
Manufacturer: Synergy Formulas, Inc
Category: homeopathic | Type: HUMAN OTC DRUG LABEL
Date: 20121204

ACTIVE INGREDIENTS: CINCHONA OFFICINALIS BARK 3 [hp_X]/1 mL; GOLDENSEAL 3 [hp_X]/1 mL; LOMATIUM DISSECTUM ROOT 3 [hp_X]/1 mL; NASTURTIUM OFFICINALE 3 [hp_X]/1 mL; NUTMEG 3 [hp_X]/1 mL; TABEBUIA IMPETIGINOSA BARK 3 [hp_X]/1 mL; CAT'S CLAW 3 [hp_X]/1 mL; MYRRH 3 [hp_X]/1 mL; GELSEMIUM SEMPERVIRENS ROOT 6 [hp_X]/1 mL; GERMANIUM SESQUIOXIDE 8 [hp_X]/1 mL; LACHESIS MUTA VENOM 8 [hp_X]/1 mL; BOS TAURUS ADRENAL GLAND 8 [hp_X]/1 mL; SUS SCROFA THYMUS 8 [hp_X]/1 mL; STRYCHNOS NUX-VOMICA SEED 12 [hp_X]/1 mL; ATROPA BELLADONNA WHOLE 12 [hp_X]/1 mL; HUMAN HERPESVIRUS 4 30 [hp_X]/1 mL; HUMAN HERPESVIRUS 3 30 [hp_X]/1 mL; MEASLES VIRUS 30 [hp_X]/1 mL; POLIOVIRUS 30 [hp_X]/1 mL; RANCID BEEF 30 [hp_X]/1 mL; HEPATITIS B VIRUS 33 [hp_X]/1 mL; HUMAN COXSACKIEVIRUS B1 15 [hp_C]/1 mL; HUMAN COXSACKIEVIRUS B4 15 [hp_C]/1 mL
INACTIVE INGREDIENTS: WATER; ALCOHOL

Drug Facts

ACTIVE INGREDIENTS

Cinchona Officinalis 3X, Hydrastis Canadensis 3X, Lomatium Dissectum 3X, Nasturtium Aquaticum 3X, Nux Moschata 3X, Tabebuia Impetiginosa 3X, Uncaria Tomentosa 3X, Myrrha 3X, 6X, Gelsemium Sempervirens 6X, Germanium Sesquioxide 8X, Lachesis Mutus 8X, Glandula Suprarenalis Bovinum 8X, 10X, 12X, Thymus Gland (Suis) 8X, 10X, 24X, Nux Vomica 12X, Belladonna 12X, 30X, Epstein-Barr Virus 30X, 60X, 200X, Herpes Zoster 30X, 60X, 200X, Morbillinum 30X, 60X, 200X, Poliomyelitis 30X, 60X, 200X, Pyrogenium 30X, 60X, 200X, Hepatitis B 33X, 60X, 200X, Coxsackie B1 15C, 30C, 100C, Coxsackie B4 15C, 30C, 100C

INDICATIONS

Temporarily relieves symptoms of viral infections.

WARNINGS

Keep out of reach of children. In case of overdose, get medical help or contact a Poison Control Center right away. If pregnant or breast-feeding, ask a health professional before use. Do not use if tamper evident seal is broken or missing.

DIRECTION

10 drops orally, 3 times a day. Consult a physician for use in children under 12 years of age.

INACTIVE INGREDIENTS

Demineralized Water, 25% Ethanol

KEEP OUT OF REACH OF CHILDREN

In case of overdose, get medical help or contact a Poison Control Center right away.

INDICATIONS AND USAGE

Temporarily relieves symptoms of viral infections.

PACKAGE LABEL DISPLAY

Synergy Formulas

VIROSODE

HOMEOPATHIC

2 FL OZ (60 ml)